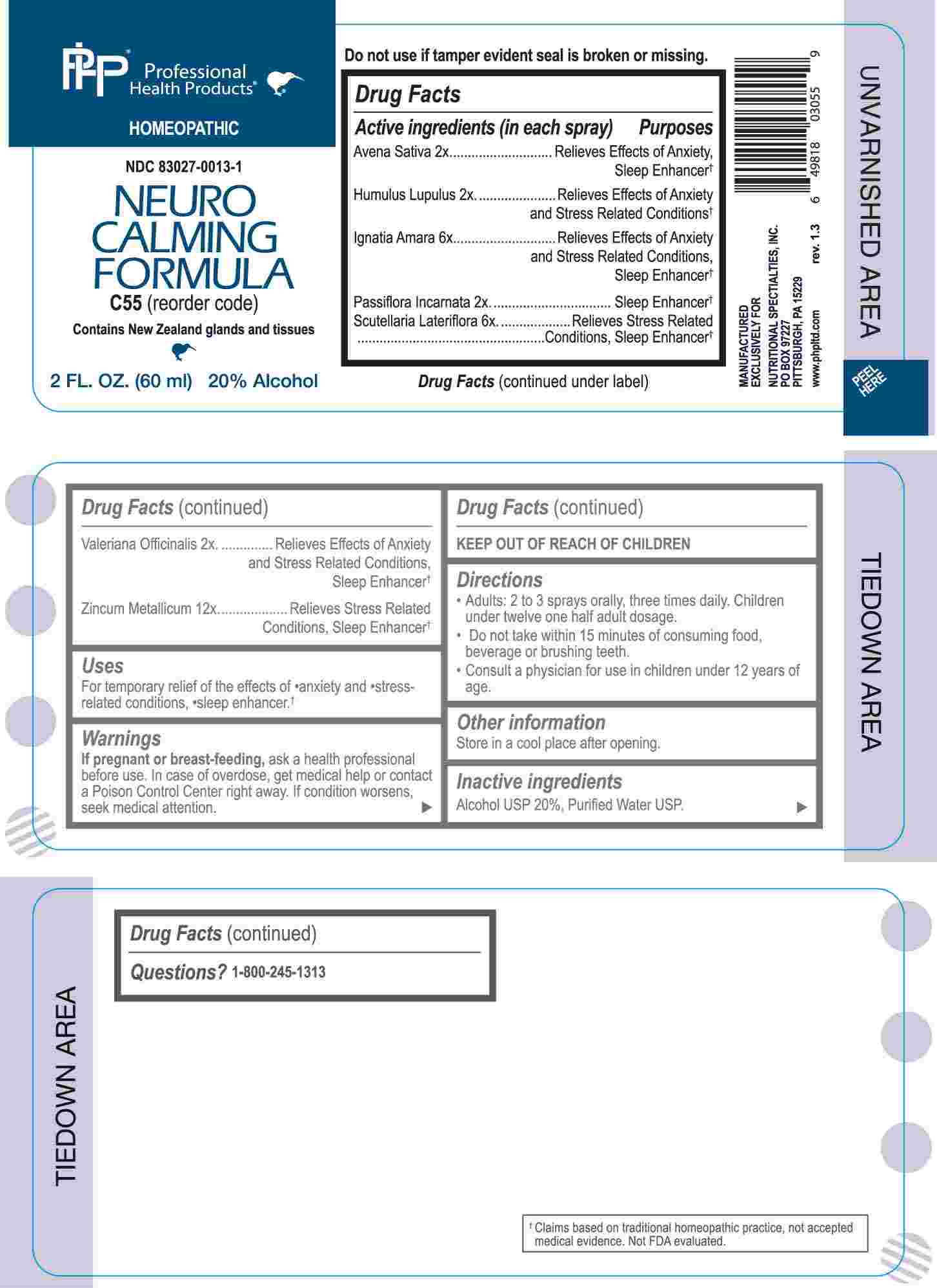 DRUG LABEL: Neuro Calming Formula
NDC: 83027-0013 | Form: SPRAY
Manufacturer: Nutritional Specialties, Inc.
Category: homeopathic | Type: HUMAN OTC DRUG LABEL
Date: 20251008

ACTIVE INGREDIENTS: AVENA SATIVA FLOWERING TOP 2 [hp_X]/1 mL; HOPS 2 [hp_X]/1 mL; PASSIFLORA INCARNATA FLOWERING TOP 2 [hp_X]/1 mL; VALERIAN 2 [hp_X]/1 mL; STRYCHNOS IGNATII SEED 6 [hp_X]/1 mL; SCUTELLARIA LATERIFLORA WHOLE 6 [hp_X]/1 mL; ZINC 12 [hp_X]/1 mL
INACTIVE INGREDIENTS: WATER; ALCOHOL

DRUG FACTS:

ACTIVE INGREDIENTS:

(in each spray) Avena Sativa 2X, Humulus Lupulus 2X, Ignatia Amara 6X, Passiflora Incarnata 2X, Scutellaria Lateriflora 6X, Valeriana Officinalis 2X, Zincum Metallicum 12X.

PURPOSE:

Avena Sativa – Relieves Effects of Anxiety, Sleep Enhancer,† Humulus Lupulus – Relieves Effects of Anxiety and Stress Related Conditions,† Ignatia Amara – Relieves Effects of Anxiety and Stress Related Conditions, Sleep Enhancer,† Passiflora Incarnata – Sleep Enhancer,† Scutellaria Lateriflora – Relieves Stress Related Conditions, Sleep Enhancer,† Valeriana Officinalis – Relieves Effects of Anxiety and Stress Related Conditions, Sleep Enhancer,† Zincum Metallicum – Relieves Stress Related Conditions, Sleep Enhancer†

USES:

For temporary relief of the effects of •anxiety and •stress-related conditions, •sleep enhancer.†

†Claims based on traditional homeopathic practice, not accepted medical evidence. Not FDA evaluated.

WARNINGS:

If pregnant or breast-feeding, ask a health professional before use.

In case of overdose, get medical help or contact a Poison Control Center right away.

If condition worsens, seek medical attention.

KEEP OUT OF REACH OF CHILDREN

Do not use if tamper evident seal is broken or missing.

Store in a cool place after opening

KEEP OUT OF REACH OF CHILDREN:

In case of overdose, get medical help or contact a Poison Control Center right away.

DIRECTIONS:

• Adults: 2 to 3 sprays orally, three times daily. Children under twelve one half adult dosage.

• Do not take within 15 minutes of consuming food, beverage or brushing teeth.

Consult a physician for use in children under 12 years of age.

INACTIVE INGREDIENTS:

Alcohol USP 20%, Purified Water USP.

QUESTIONS:

MANUFACTURED EXCLUSIVELY FOR

NUTRITIONAL SPECIALTIES, INC.

PO BOX 97227

PITTSBURG, PA 15229

www.phpltd.com

1-800-245-1313

PACKAGE LABEL DISPLAY:

Professional

Health Products

HOMEOPATHIC

NDC 83027-0013-1

NEURO CALMING

FORMULA

2 FL. OZ (60 ml)